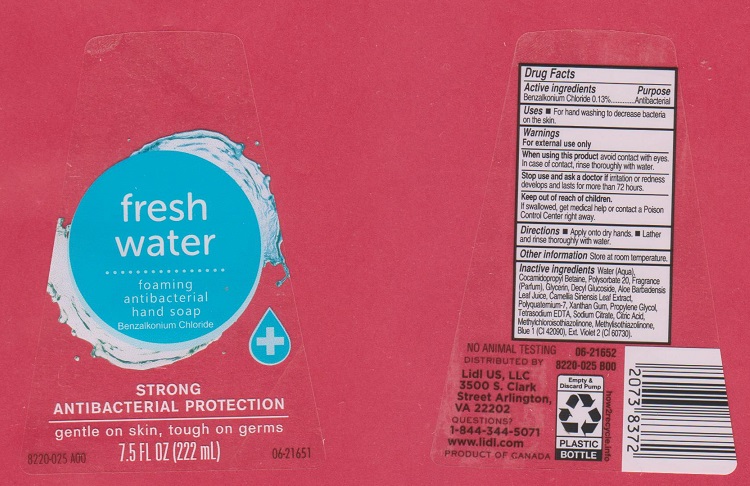 DRUG LABEL: Fresh Water Antibacterial Foaming Hand
NDC: 63148-110 | Form: SOAP
Manufacturer: Apollo Health and Beauty Care Inc.
Category: otc | Type: HUMAN OTC DRUG LABEL
Date: 20170330

ACTIVE INGREDIENTS: BENZALKONIUM CHLORIDE 1.3 mg/1 mL
INACTIVE INGREDIENTS: WATER; COCAMIDOPROPYL BETAINE; POLYSORBATE 20; GLYCERIN; DECYL GLUCOSIDE; ALOE VERA LEAF; GREEN TEA LEAF; POLYQUATERNIUM-7 (70/30 ACRYLAMIDE/DADMAC; 1600000 MW); XANTHAN GUM; PROPYLENE GLYCOL; EDETATE SODIUM; SODIUM CITRATE; CITRIC ACID MONOHYDRATE; METHYLCHLOROISOTHIAZOLINONE; METHYLISOTHIAZOLINONE; FD&C BLUE NO. 1; EXT. D&C VIOLET NO. 2

Drug Facts

Active ingredients

Benzalkonium Chloride 0.13%

Purpose

Antibacterial

Uses

For hand washing to decrease bacteria on the skin.

Warnings

For external use only.

When using this product

avoid contact with eyes. In case of contact, rinse thoroughly with water.

Stop use and ask a doctor if

irritation or redness develops and lasts for more than 72 hours.

Keep out of reach of children.

If swallowed, get medical help or contact a Poison Control Center immediately.

Directions

- Apply onto dry hands.
- Lather and rinse thoroughly with water.

Other information

Store at room termpature

Inactive ingredients

Water (Aqua), Cocamdiopropyl Betaine, Polysorbate 20, Fragrance (Parfum), Glycerin, Decyl Glucoside, Aloe Barbadensis Leaf Juice, Camellia Sinensis Leaf Extract, Polyquaternium-7, Xanthan Gum, Propylene Glycol, Tetrasodium EDTA, Sodium Citrate, Citric Acid, Methylchloroisothiazolinone, Methylisothiazolinone, Blue 1 (CI 42090), Ext. Violet 2 (CI 60730).